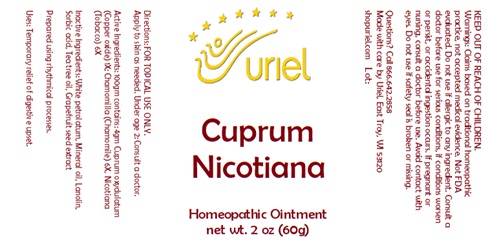 DRUG LABEL: Cuprum Nicotiana
NDC: 48951-3144 | Form: OINTMENT
Manufacturer: Uriel Pharmacy Inc.
Category: homeopathic | Type: HUMAN OTC DRUG LABEL
Date: 20241206

ACTIVE INGREDIENTS: CUPRIC OXIDE 1 [hp_X]/1 g; MATRICARIA RECUTITA 6 [hp_X]/1 g; TOBACCO LEAF 6 [hp_X]/1 g
INACTIVE INGREDIENTS: PETROLATUM; LANOLIN; MINERAL OIL; SORBIC ACID; TEA TREE OIL; CITRUS PARADISI SEED

Cuprum Nicotiana

INDICATIONS AND USAGE

Directions: FOR TOPICAL USE ONLY.

DOSAGE AND ADMINISTRATION

Apply to skin as needed. Under age 2: Consult a doctor.

ACTIVE INGREDIENT

Active Ingredients: 100gm contains: 4gm Cuprum oxydulatum (Copper oxide) 1X; Chamomilla (Chamomile) 6X, Nicotiana (Tobacco) 6X

INACTIVE INGREDIENT

Inactive Ingredients: White petrolatum, Lanolin, Mineral oil, Sorbic acid, Tea tree oil, Grapefruit seed extract

Prepared using rhythmical processes.

PURPOSE

Uses: Temporary relief of digestive upset.

KEEP OUT OF REACH OF CHILDREN.

Warnings: FOR EXTERNAL USE ONLY.
Claims based on traditional homeopathic practice, not accepted medical evidence. Not FDA evaluated. Do not use if allergic to any ingredient. Consult a doctor before use for serious conditions, if conditions worsen or persist, or accidental ingestion occurs. If pregnant or nursing consult a doctor before use. Avoid contact with eyes. Do not use if safety seal is broken or missing.

Questions? Call 866.642.2858
Made with care by Uriel, East Troy, WI 53120
shopuriel.com Lot: